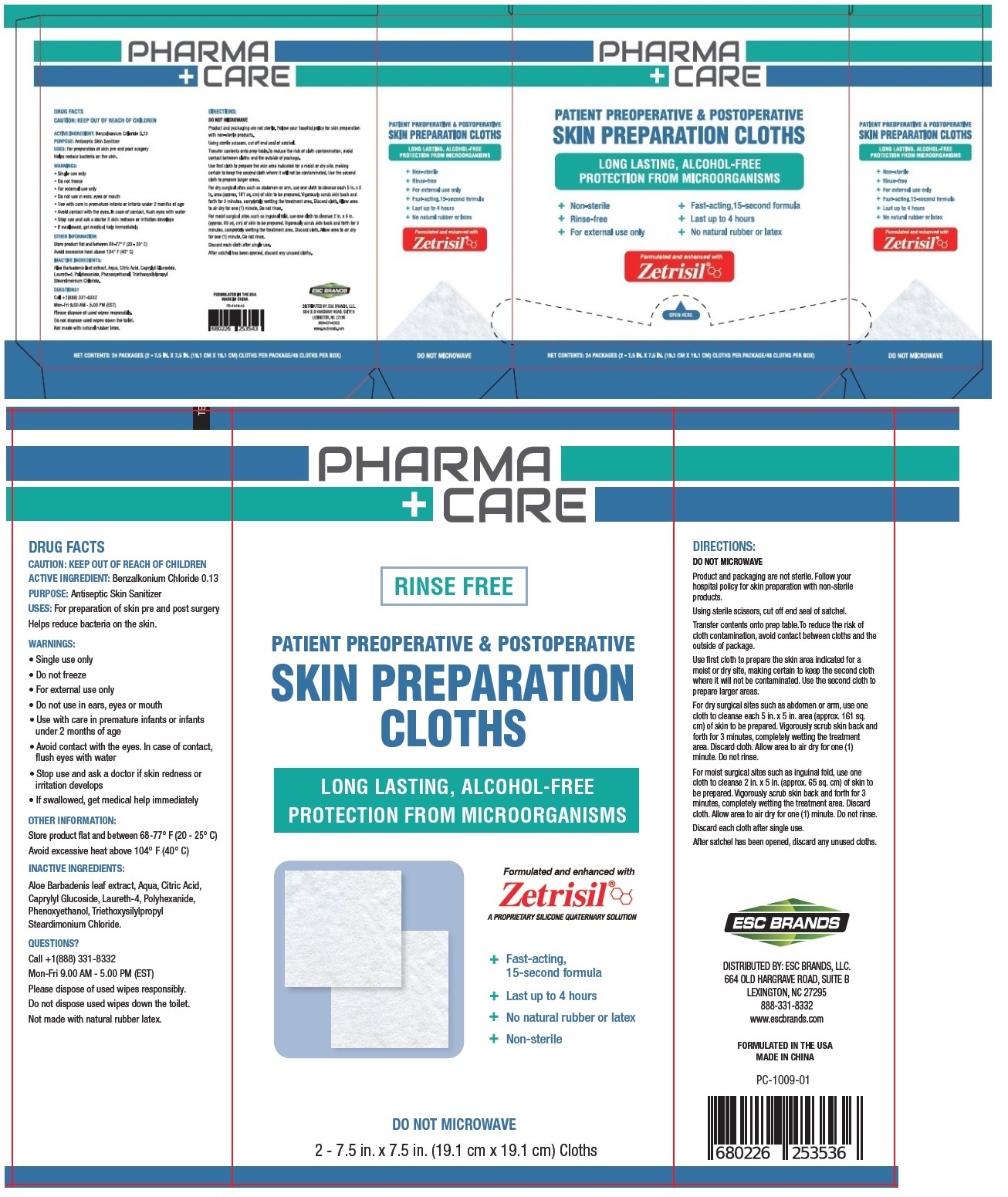 DRUG LABEL: Pharma-Care Skin Preparation Cloths
NDC: 71884-015 | Form: CLOTH
Manufacturer: Enviro Specialty Chemicals Inc
Category: otc | Type: HUMAN OTC DRUG LABEL
Date: 20241231

ACTIVE INGREDIENTS: BENZALKONIUM CHLORIDE 0.13 g/100 mL
INACTIVE INGREDIENTS: ALOE VERA LEAF; WATER; CITRIC ACID MONOHYDRATE; CAPRYLYL GLUCOSIDE; LAURETH-4; POLIHEXANIDE; PHENOXYETHANOL; TRIETHOXYSILYLPROPYL STEARDIMONIUM CHLORIDE

PHARMA + CARE PATIENT PREOPERATIVE & POSTOPERATIVE SKIN PREPARATION CLOTHS

ACTIVE INGREDIENT: Benzalkonium Chloride 0.13

PURPOSE: Antiseptic Skin Sanitizer

INDICATIONS AND USAGE

USES: For preparation of skin pre and post surgery

Helps reduce bacteria on the skin.

WARNINGS:

• Single use only

• Do not freeze

• For external use only

• Do not use in ears, eyes or mouth

• Use with care in premature infants or infants under 2 months of age

• Avoid contact with the eyes. In case of contact, flush eyes with water

• Stop use and ask a doctor if skin redness or irritation develops

• If swallowed, get medical help immediately

OTHER INFORMATION:

Store product flat and between 68-77° F (20 - 25° C)

Avoid excessive heat above 104° F (40° C)

INACTIVE INGREDIENTS:

Aloe Barbadensis leaf extract, Aqua, Citric Acid, Caprylyl Glucoside, Laureth-4, Polyhexanide, Phenoxyethanol, Triethoxysilylpropyl Steardimonium Chloride.

QUESTIONS?

Call +1(888) 331-8332

Mon-Fri 9.00 AM - 5.00 PM (EST)

DIRECTIONS:

DO NOT MICROWAVE

Product and packaging are not sterile. Follow your hospital policy for skin preparation with non-sterile products.

Using sterile scissors, cut off end seal of satchel.

Transfer contents onto prep table.To reduce the risk of cloth contamination, avoid contact between cloths and the outside of package.

Use first cloth to prepare the skin area indicated for a moist or dry site, making certain to keep the second cloth where it will not be

contaminated. Use the second cloth to prepare larger areas.

For dry surgical sites such as abdomen or arm, use one cloth to cleanse each 5 in. x 5 in. area (approx. 161 sq. cm) of skin to be prepared.

Vigorously scrub skin back and forth for 3 minutes, completely wetting the treatment area. Discard cloth. Allow area to air dry for one (1)

minute. Do not rinse.

For moist surgical sites such as inguinal fold, use one cloth to cleanse 2 in. x 5 in. (approx. 65 sq. cm) of skin to be prepared. Vigorously scrub skin back and forth for 3 minutes, completely wetting the treatment area. Discard cloth. Allow area to air dry for one (1) minute. Do not rinse.

Discard each cloth after single use.

After satchel has been opened, discard any unused cloths.

RINSE FREE

LONG LASTING, ALCOHOL-FREE

PROTECTION FROM MICROORGANISMS

Formulated and enhanced with

Zetrisil

A PROPRIETARY SILICONE QUATERNARY SOLUTION

+ Fast-acting, 15-second formula

+ Last up to 4 hours

+ No natural rubber or latex

+ Non-sterile

DO NOT MICROWAVE

Please dispose of used wipes responsibly.

Do not dispose used wipes down the toilet.

Not made with natural rubber latex.

ESC BRANDS

DISTRIBUTED BY: ESC BRANDS, LLC.

OLD HARGRAVE ROAD, SUITE B

LEXINGTON, NC 27295

888-331-8332

www.escbrands.com

FORMULATED IN THE USA

MADE IN CHINA